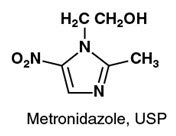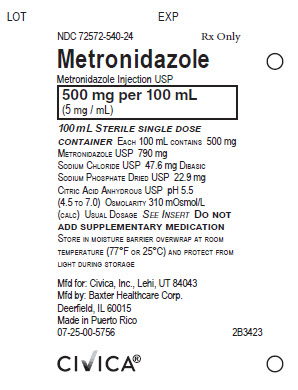 DRUG LABEL: Metronidazole
NDC: 72572-540 | Form: INJECTION, SOLUTION
Manufacturer: Civica, Inc.
Category: prescription | Type: HUMAN PRESCRIPTION DRUG LABEL
Date: 20251121

ACTIVE INGREDIENTS: METRONIDAZOLE 500 mg/100 mL
INACTIVE INGREDIENTS: SODIUM CHLORIDE 790 mg/100 mL; SODIUM PHOSPHATE, DIBASIC 47.6 mg/100 mL; ANHYDROUS CITRIC ACID 22.9 mg/100 mL; WATER

Metronidazole Injection, USP
in Plastic Container
VIAFLEX Plus Container

To reduce the development of drug-resistant bacteria and maintain the effectiveness of Metronidazole Injection and other antibacterial drugs, Metronidazole Injection should be used only to treat or prevent infections that are proven or strongly suspected to be caused by bacteria.

WARNING

Metronidazole has been shown to be carcinogenic in mice and rats (see PRECAUTIONS). Unnecessary use of the drug should be avoided. Its use should be reserved for the conditions described in the INDICATIONS AND USAGE section below.

DESCRIPTION

Metronidazole Injection, USP, is a parenteral formulation of the synthetic nitroimidazole antibacterial agent 2-methyl-5-nitro-1H-imidazole-1-ethanol.

Metronidazole Injection, USP, in 100 mL VIAFLEX Plus single dose plastic container, is a sterile, nonpyrogenic, iso-osmotic, buffered solution of 500 mg Metronidazole, USP, 790 mg Sodium Chloride, USP, 47.6 mg Dibasic Sodium Phosphate Dried, USP and 22.9 mg Citric Acid Anhydrous, USP. Metronidazole Injection, USP has an osmolarity of 310 mOsmol/L (calc) and a pH of 5.5 (4.5 to 7.0). Each container contains 14 mEq of sodium.

The plastic container is fabricated from a specially formulated polyvinyl chloride plastic. Water can permeate from inside the container into the overwrap in amounts insufficient to affect the solution significantly. Solutions in contact with the plastic container can leach out certain of its chemical components in very small amounts within the expiration period, e.g., di-2-ethylhexyl phthalate (DEHP), up to 5 parts per million. However, the safety of the plastic has been confirmed in tests in animals according to USP biological tests for plastic containers as well as by tissue culture toxicity studies.

CLINICAL PHARMACOLOGY

In patients treated with intravenous metronidazole, using a dosage regimen of 15 mg/kg loading dose followed 6 hours later by 7.5 mg/kg every 6 hours, the average peak steady-state plasma concentrations (Cmax) and trough concentrations (Cmin) were 25 mcg/mL and 18 mcg/mL, respectively. Plasma concentrations of metronidazole are proportional to the administered dose. An eight-hour intravenous infusion of 100 mg to 4,000 mg of metronidazole in normal subjects showed a linear relationship between dose and peak plasma concentration. The average elimination half-life of metronidazole in healthy subjects is eight hours.

Distribution

Metronidazole is the major component appearing in the plasma, with lesser quantities of metabolites also being present. Less than 20% of the circulating metronidazole is bound to plasma proteins. Metronidazole appears in cerebrospinal fluid, saliva and breast milk in concentrations similar to those found in plasma. Bactericidal concentrations of metronidazole have also been detected in pus from hepatic abscesses.

Following a single intravenous dose of metronidazole 500 mg, 4 healthy subjects who underwent gastrointestinal endoscopy had peak gastric juice metronidazole concentrations of 5 to 6 mcg/mL at one hour post-dose. In patients receiving intravenous metronidazole in whom gastric secretions are continuously removed by nasogastric aspiration, sufficient metronidazole may be removed in the aspirate to cause a reduction in serum levels.

Metabolism

The metabolites of metronidazole result primarily from side-chain oxidation [1-(ß-hydroxyethyl)-2-hydroxymethyl-5-nitroimidazole and 2-methyl-5-nitroimidazole-1-yl-acetic acid] and glucuronide conjugation. Both the parent compound and the hydroxyl metabolite possess in vitro antimicrobial activity.

Excretion

The major route of elimination of metronidazole and its metabolites is via the urine (60-80% of the dose), with approximately 20% of the amount excreted appearing as unchanged metronidazole. Renal clearance of metronidazole is approximately 10 mL/min/1.73 m^2. Fecal excretion accounts for 6-15% of the dose.

Renal Impairment

Decreased renal function does not alter the single-dose pharmacokinetics of metronidazole.

Subjects with end-stage renal disease (ESRD; CLCR= 8.1±9.1 mL/min) and who received a single intravenous infusion of metronidazole 500 mg had no significant change in metronidazole pharmacokinetics but had 2-fold higher Cmax of hydroxy-metronidazole and 5-fold higher Cmax of metronidazole acetate, compared to healthy subjects with normal renal function (CLCR= 126 ± 16 mL/min). Thus, on account of the potential accumulation of metronidazole metabolites in ESRD patients, monitoring for metronidazole associated adverse events is recommended (see PRECAUTIONS).

Effect of Dialysis

Following a single intravenous infusion or oral dose of metronidazole 500 mg, the clearance of metronidazole was investigated in ESRD subjects undergoing hemodialysis or continuous ambulatory peritoneal dialysis (CAPD). A hemodialysis session lasting for 4 to 8 hours removed 40% to 65% of the administered metronidazole dose, depending on the type of the dialyzer membrane used and the duration of the dialysis session. If the administration of metronidazole cannot be separated from the dialysis session, supplementation of metronidazole dose following hemodialysis should be considered (see DOSAGE AND ADMINISTRATION). A peritoneal dialysis session lasting for 7.5 hours removed approximately 10% of the administered metronidazole dose. No adjustment in metronidazole dose is needed in ESRD patients undergoing CAPD.

Hepatic Impairment

Following a single intravenous infusion of 500 mg metronidazole, the mean AUC24 of metronidazole was higher by 114% in patients with severe (Child-Pugh C) hepatic impairment, and by 54% and 53% in patients with a mild (Child-Pugh A) and moderate (Child-Pugh B) hepatic impairment, respectively, compared to healthy control subjects. There were no significant changes in the AUC24 of hydroxy-metronidazole in these hepatically impaired patients. A reduction in metronidazole dosage by 50% is recommended in patients with severe (Child-Pugh C) hepatic impairment (see DOSAGE AND ADMINISTRATION). No dosage adjustment is needed for patients with mild to moderate hepatic impairment. Patients with mild to moderate hepatic impairment should be monitored for metronidazole associated adverse events (see PRECAUTIONS and DOSAGE AND ADMINISTRATION).

Geriatric Patients

Following a single 500 mg oral or IV dose of metronidazole, subjects >70 years old with no apparent renal or hepatic dysfunction had a 40% to 80% higher mean AUC of hydroxy-metronidazole (active metabolite), with no apparent increase in the mean AUC of metronidazole (parent compound), compared to young healthy controls < 40 years old. In geriatric patients, monitoring for metronidazole associated adverse events is recommended (see PRECAUTIONS).

Pediatric Patients

In one study newborn infants appeared to demonstrate diminished capacity to eliminate metronidazole. The elimination half-life, measured during the first three days of life, was inversely related to gestational age. In infants whose gestational ages were between 28 and 40 weeks, the corresponding elimination half-lives ranged from 109 to 22.5 hours.

Two other trials included infants 23-48 weeks post-menstrual age, (0-80 days postnatal age) with complicated intra-abdominal infections. Clearance increased with increasing post-menstrual age, while volume of distribution and half-life decreased (see PRECAUTIONS, Pediatric Use and DOSAGE AND ADMINISTRATION).

Microbiology

Mechanism of Action

Metronidazole, a nitroimidazole, exerts antibacterial effects in an anaerobic environment against most obligate anaerobes. Once metronidazole enters the organism by passive diffusion and is activated in the cytoplasm of susceptible anaerobic bacteria, it is reduced; this process includes intra-cellular electron transport proteins such as ferredoxin, transfer of an electron to the nitro group of the metronidazole, and formation of a short-lived nitroso free radical. Because of this alteration of the metronidazole molecule, a concentration gradient is created and maintained which promotes the drug’s intracellular transport. The reduced form of metronidazole and free radicals can interact with DNA leading to inhibition of DNA synthesis and DNA degradation leading to death of bacteria. The precise mechanism of action of metronidazole is unclear.

Drug Resistance

A potential for development of resistance exists against metronidazole.

Resistance may be due to multiple mechanisms that include decreased uptake of the drug, altered reduction efficiency, overexpression of the efflux pumps, inactivation of the drug, and/or increased DNA damage repair.

Metronidazole does not possess any clinically relevant activity against facultative anaerobes or obligate aerobes.

Activity In Vitro and in Clinical Infections

Metronidazole has been shown to be active against most isolates of the following bacteria both in vitro and in clinical infections as described in the INDICATIONS AND USAGE section.

Gram-positive anaerobes

Clostridium species
Eubacterium species
Peptococcus species
Peptostreptococcus species

Gram-negative anaerobes

Bacteroides fragilis group (B. fragilis, B. distasonis, B. ovatus, B. thetaiotaomicron, B. vulgatus)
Fusobacterium species

The following in vitro data are available, but their clinical significance is unknown.

Metronidazole exhibits in vitro minimal inhibitory concentrations (MIC’s) of 8 mcg/mL or less against most (≥ 90%) isolates of the following bacteria; however, the safety and effectiveness of metronidazole in treating clinical infections due to these bacteria have not been established in adequate and well-controlled clinical trials.

Gram-negative anaerobes

Bacteroides fragilis group (B. caccae, B. uniformis)
Prevotella species (P. bivia, P. buccae, P. disiens)

Susceptibility Tests

For specific information regarding susceptibility test interpretive criteria and associated test methods and quality control standards recognized by FDA for this drug, please see: http://www.fda.gov/STIC.

INDICATIONS AND USAGE

Treatment of Anaerobic Bacterial Infections

Metronidazole Injection is indicated in the treatment of serious infections caused by susceptible anaerobic bacteria. Indicated surgical procedures should be performed in conjunction with Metronidazole Injection therapy. In a mixed aerobic and anaerobic infection, antibacterial drugs appropriate for the treatment of the aerobic infection should be used in addition to Metronidazole Injection.

Metronidazole Injection is effective in Bacteroides fragilis infections resistant to clindamycin, chloramphenicol and penicillin.

- Intra-Abdominal Infections, including peritonitis, intra-abdominal abscess and liver abscess, caused by Bacteroides species including the B. fragilis group (B. fragilis, B. distasonis, B. ovatus, B. thetaiotaomicron, B. vulgatus), Clostridium species, Eubacterium species, Peptococcus species and Peptostreptococcus species in adults and pediatric patients less than 4 months of age.
- Skin and Skin Structure Infections caused by Bacteroides species including the B. fragilis group, Clostridium species, Peptococcus species, Peptostreptococcus species and Fusobacterium species in adults.
- Gynecologic Infections, including endometritis, endomyometritis, tubo-ovarian abscess and postsurgical vaginal cuff infection, caused by Bacteroides species including the B. fragilis group, Clostridium species, Peptococcus species, Peptostreptococcus species and Fusobacterium species in adults.
- Bacterial Septicemia caused by Bacteroides species including the B. fragilis group and Clostridium species in adults.
- Bone and Joint Infections, as adjunctive therapy, caused by Bacteroides species including the B. fragilis group in adults.
- Central Nervous System (CNS) Infections, including meningitis and brain abscess, caused by Bacteroides species including the B. fragilis group in adults.
- Lower Respiratory Tract Infections, including pneumonia, empyema and lung abscess, caused by Bacteroides species including the B. fragilis group in adults.
- Endocarditis caused by Bacteroides species including the B. fragilis group in adults.

Prophylaxis Indication

The prophylactic administration of Metronidazole Injection preoperatively, intraoperatively and postoperatively may reduce the incidence of postoperative infection in adult patients undergoing elective colorectal surgery which is classified as contaminated or potentially contaminated. Prophylactic use of Metronidazole Injection should be discontinued within 12 hours after surgery. If there are signs of infection, specimens for cultures should be obtained for the identification of the causative organism(s) so that appropriate therapy may be given (see DOSAGE AND ADMINISTRATION).

Usage

To reduce the development of drug-resistant bacteria and maintain the effectiveness of Metronidazole Injection and other antibacterial drugs, Metronidazole Injection should be used only to treat or prevent infections that are proven or strongly suspected to be caused by susceptible bacteria. When culture and susceptibility information are available, they should be considered in selecting or modifying antibacterial therapy. In the absence of such data, local epidemiology and susceptibility patterns may contribute to the empiric selection of therapy.

CONTRAINDICATIONS

- Hypersensitivity
  Metronidazole Injection is contraindicated in patients with a prior history of hypersensitivity to metronidazole or other nitroimidazole derivatives.
- Psychotic Reaction with Disulfiram
  Use of oral metronidazole is associated with psychotic reactions in alcoholic patients who were using disulfiram concurrently. Do not administer metronidazole to patients who have taken disulfiram within the last two weeks (see PRECAUTIONS-Drug Interactions).
- Interaction with Alcohol
  Use of oral metronidazole is associated with a disulfiram-like reaction to alcohol, including abdominal cramps, nausea, vomiting, headaches, and flushing. Discontinue consumption of alcohol or products containing propylene glycol during and for at least three days after therapy with metronidazole (see PRECAUTIONS-Drug Interactions).
- Cockayne Syndrome
  Metronidazole Injection is contraindicated in patients with Cockayne syndrome. Severe irreversible hepatotoxicity/acute liver failure with fatal outcomes have been reported after initiation of metronidazole in patients with Cockayne syndrome (see ADVERSE REACTIONS).

WARNINGS

Severe cutaneous adverse reactions (SCARs) including toxic epidermal necrolysis (TEN), Stevens-Johnson syndrome (SJS), drug reaction with eosinophilia and systemic symptoms (DRESS), and acute generalized exanthematous pustulosis (AGEP) have been reported with the use of metronidazole. Symptoms can be serious and potentially life threatening. If symptoms or signs of SCARs develop, discontinue Metronidazole injection immediately and institute appropriate therapy.

Central and Peripheral Nervous System Effects

Severe neurological disturbances, including encephalopathy, cerebellar symptoms, convulsive seizures, peripheral neuropathy, optic neuropathy, and aseptic meningitis, have been reported in patients treated with metronidazole.

Encephalopathy associated with metronidazole may manifest as confusion or decreased level of consciousness, and is associated with widespread lesions on magnetic resonance imaging (MRI) of the brain. Cerebellar toxicity associated with metronidazole may manifest as ataxia, dizziness, dysarthria, nystagmus and saccadic pursuit and is accompanied by T2 flair lesions within the dentate nuclei seen on MRI. Cerebellar toxicity may concurrently occur with encephalopathy, peripheral neuropathy or seizures. CNS symptoms and CNS lesions are generally reversible within days to weeks upon discontinuation of Metronidazole Injection. Peripheral neuropathy, usually symmetric and mainly of sensory type is characterized by numbness or paresthesia of an extremity. Symptoms may be prolonged after drug discontinuation. Aseptic meningitis may occur within hours of dose administration and generally resolve after metronidazole therapy is discontinued (see ADVERSE REACTIONS).

Advise patients to report neurologic symptoms that occur during metronidazole administration. Discontinue metronidazole treatment if any abnormal neurologic symptoms occur such as ataxia, dizziness, confusion or any other CNS adverse reaction (see ADVERSE REACTIONS).

PRECAUTIONS

General

Hepatic Impairment

Patients with hepatic impairment metabolize metronidazole slowly, with resultant accumulation of metronidazole and increase the plasma concentrations. Reduce the dose of Metronidazole Injection by 50% in patients with severe hepatic impairment (Child-Pugh C). For patients with mild to moderate hepatic impairment, no dosage adjustment is needed but these patients should be monitored for metronidazole associated adverse events (see CLINICAL PHARMACOLOGY and DOSAGE AND ADMINISTRATION).

Patients with severe hepatic encephalopathy metabolize metronidazole slowly, with resultant accumulation of metronidazole. This may cause exacerbation of CNS adverse effects. Reduce the dose of Metronidazole Injection as necessary.

Renal Impairment

For patients with mild to moderate renal impairment dose adjustment is not considered necessary as elimination half-life is not significantly altered. In patients with severe renal impairment or end stage of renal disease, metronidazole and metronidazole metabolites may accumulate significantly because of reduced urinary excretion in those patients. Monitoring for metronidazole associated adverse events is recommended when metronidazole is administered in patients with severe renal impairment or end stage of renal disease who are not undergoing hemodialysis (see CLINICAL PHARMACOLOGY).

Hemodialysis removes significant amounts of metronidazole and its metabolites from systemic circulation. Therefore, supplementation of metronidazole following a hemodialysis session may be necessary.

Patients receiving peritoneal dialysis should be monitored for signs of toxicity due to the potential accumulation of metronidazole metabolites.

Fungal Superinfections

Known or previously unrecognized candidiasis may present more prominent symptoms during therapy with Metronidazole Injection and requires treatment with a candicidal agent.

Use in Patients with Blood Dyscrasias

Metronidazole is a nitroimidazole, and should be used with care in patients with evidence of or history of blood dyscrasia. Agranulocytosis, leukopenia and neutropenia have been associated with metronidazole administration. Monitor complete blood count in these patients.

Monitoring for Leukopenia

Monitoring of complete blood count (CBC) is recommended before, during, and after prolonged or repeated courses of metronidazole therapy.

Sodium Retention

Metronidazole Injection contains 790 mg of sodium per 100 mL. Care should be taken when administering Metronidazole Injection to patients receiving a controlled sodium diet or corticosteroids or to patients predisposed to edema.

Drug-Resistant Bacteria

Prescribing Metronidazole Injection in the absence of a proven or strongly suspected bacterial infection or a prophylactic indication is unlikely to provide benefit to the patient and increases the risk of the development of drug-resistant bacteria.

Information for Patients

- Interaction with Alcohol
  Discontinue consumption of alcoholic beverages or products containing propylene glycol while taking Metronidazole Injection and for at least three days afterward because abdominal cramps, nausea, vomiting, headaches, and flushing may occur (see CONTRAINDICATIONS, PRECAUTIONS-Drug Interactions).
- Treatment of Bacterial Infections
  Patients should be counseled that antibacterial drugs including Metronidazole Injection should only be used to treat bacterial infections. They do not treat viral infections (e.g., the common cold). When Metronidazole Injection is prescribed to treat a bacterial infection, patients should be told that although it is common to feel better early in the course of therapy, the medication should be taken exactly as directed. Skipping doses or not completing the full course of therapy may (1) decrease the effectiveness of the immediate treatment and (2) increase the likelihood that bacteria will develop resistance and will not be treatable by Metronidazole Injection or other antibacterial drugs in the future.
- Severe Cutaneous Adverse Reactions
  Advise patients that Metronidazole Injection may increase the risk of serious and sometimes fatal dermatologic reactions, including toxic epidermal necrolysis (TEN), Stevens-Johnson syndrome (SJS), and drug reaction with eosinophilia and systemic symptoms (DRESS). Instruct the patient to be alert for skin rash, blisters, fever or other signs and symptoms of these hypersensitivity reactions. Advise patients to stop Metronidazole Injection immediately if they develop any type of rash and seek medical attention.

Drug Interactions

- Disulfiram
  Psychotic reactions and confusion have been reported in alcoholic patients who are using metronidazole and disulfiram concurrently. Do not administer Metronidazole Injection to patients who have taken disulfiram within the last two weeks (see CONTRAINDICATIONS).
- Alcoholic Beverages
  Abdominal cramps, nausea, vomiting, headaches, tachycardia and flushing may occur if alcoholic beverages or products containing propylene glycol are consumed during or following metronidazole therapy. Discontinue consumption of alcohol or products containing propylene glycol before, during and up to 72 hours after therapy with Metronidazole Injection (see CONTRAINDICATIONS).
- Warfarin and other Oral Anticoagulants
  Metronidazole has been reported to potentiate the anticoagulant effect of warfarin and other oral coumarin anticoagulants, resulting in a prolongation of prothrombin time and increased risk of hemorrhages. When Metronidazole Injection is prescribed for patients on this type of anticoagulant therapy, prothrombin time and international normalized ratio (INR) should be carefully monitored and their anticoagulant dose adjusted accordingly. Monitor patients for signs and symptoms of bleeding.
- Lithium
  In patients stabilized on relatively high doses of lithium, short-term metronidazole therapy has been associated with elevation of serum lithium and, in a few cases, signs of lithium toxicity. Lithium toxicity may lead to renal damage. Frequent monitoring of serum lithium and serum creatinine levels is necessary.
- Busulfan
  Metronidazole has been reported to increase plasma concentrations of busulfan, which can result in an increased risk for serious busulfan toxicity such as sinusoidal obstruction syndrome, gastrointestinal mucositis, and hepatic veno-occlusive disease. Metronidazole Injection should not be administered concomitantly with busulfan unless the benefit outweighs the risk. If no therapeutic alternatives to metronidazole are available, and concomitant administration with busulfan is medically needed, frequent monitoring of busulfan plasma concentration should be performed and the busulfan dose should be adjusted accordingly.
- Drugs that Inhibit CYP450 Enzymes
  The simultaneous administration of drugs that decrease microsomal liver enzyme activity, such as cimetidine, may decrease metabolism and reduce plasma clearance of metronidazole which may result in metronidazole toxicity.
- Drugs that Induce CYP450 Enzymes
  The simultaneous administration of drugs that induce microsomal liver enzyme activity, such as phenytoin or phenobarbital, may accelerate the elimination of metronidazole and therefore decrease its efficacy.
- Cytochrome P450 3A4 (CYP3A4) substrates
  Concomitant use of Metronidazole Injection and CYP3A4 substrates (e.g., amiodarone, tacrolimus, cyclosporine, carbamazepine, phenytoin, and quinidine) may increase respective CYP3A4-substrate plasma levels. Monitoring of plasma concentrations of CYP3A4 substrates may be necessary.
- 5-Fluorouracil
  Metronidazole Injection decreases the clearance of 5-fluorouracil and may therefore cause 5-fluorouracil toxicity.
- Vecuronium
  Metronidazole Injection may potentiate the effects of vecuronium.
- Drugs that Prolong the QT interval
  QT prolongation has been reported, particularly when metronidazole was administered with drugs with the potential for prolonging the QT interval.
- Drug/Laboratory Test Interactions
  Metronidazole may interfere with certain types of determinations of serum chemistry values, such as aspartate aminotransferase (AST, SGOT), alanine aminotransferase (ALT, SGPT), lactate dehydrogenase (LDH), triglycerides and glucose hexokinase. Metronidazole causes an increase in ultraviolet absorbance at 340 nm resulting in falsely decreased values.

Carcinogenesis, Mutagenesis, Impairment of Fertility

Tumors affecting the liver, lung, mammary and lymphatic tissues have been detected in several studies of metronidazole in rats and mice, but not hamsters.

Pulmonary tumors have been observed in all six reported studies in the mouse, including one study in which the animals were dosed on an intermittent schedule (administration during every fourth week only). Malignant tumors were increased in male mice treated at approximately 1500 mg/m^2 (similar to the maximum recommended daily dose, based on body surface area comparisons). Malignant lymphomas and pulmonary neoplasms were also increased with lifetime feeding of the drug to mice. Mammary and hepatic tumors were increased among female rats administered oral metronidazole compared to concurrent controls. Two lifetime tumorigenicity studies in hamsters have been performed and reported to be negative.

Metronidazole has shown mutagenic activity in in vitro assay systems including the Ames test. Studies in mammals in vivo have failed to demonstrate a potential for genetic damage.

Metronidazole failed to produce any adverse effects on fertility or testicular function in male rats at doses up to 400 mg/kg/day (approximately 2 times the maximum recommended daily dose based on body surface area comparison) for 28 days. However, rats treated at the same dose for 6 weeks, or longer were infertile and showed severe degeneration of the seminiferous epithelium in the testes as well as marked decreases in testicular spermatid counts and epididymal sperm counts. Fertility was restored in most rats after an eight week, drug-free recovery period.

Fertility studies have been performed in male mice at doses up to six times the maximum recommended human dose based on mg/m^2 and have revealed no evidence of impaired fertility. However, metronidazole was associated with reversible adverse effects on the male reproductive system (significantly decreased testes and epididymides weight, decreased sperm viability, and increased the incidence of abnormal sperm).

Pregnancy

Teratogenic Effects

There are no adequate and well-controlled studies of Metronidazole Injection in pregnant women. There are published data from case-control studies, cohort studies, and 2 meta-analyses that include more than 5000 pregnant women who used metronidazole during pregnancy. Many studies included first trimester exposures. One study showed an increased risk of cleft lip, with or without cleft palate, in infants exposed to metronidazole in utero; however, these findings were not confirmed. In addition, more than ten randomized, placebo-controlled clinical trials enrolled more than 5000 pregnant women to assess the use of antibiotic treatment (including metronidazole) for bacterial vaginosis on the incidence of preterm delivery. Most studies did not show an increased risk for congenital anomalies or other adverse fetal outcomes following metronidazole exposure during pregnancy. Three studies conducted to assess the risk of infant cancer following metronidazole exposure during pregnancy did not show an increased risk; however, the ability of these studies to detect such a signal was limited.

Metronidazole crosses the placental barrier and its effects on the human fetal organogenesis are not known. Reproduction studies have been performed in rats, rabbits and mice at doses similar to the maximum recommended daily dose based on body surface area comparisons. There was no evidence of harm to the fetus due to metronidazole.

Healthcare provider should carefully consider the potential risks and benefits for each specific patient before prescribing Metronidazole Injection.

Nursing Mothers

Metronidazole is present in human milk at concentrations similar to maternal serum levels, and infant serum levels can be close to or comparable to infant therapeutic levels. Because of the potential for tumorigenicity shown for metronidazole in mouse and rat studies, a decision should be made whether to discontinue nursing or to discontinue the drug, taking into account the importance of the drug to the mother. Alternatively, a nursing mother may choose to pump and discard human milk for the duration of metronidazole therapy, and for 24 hours after therapy ends and feed her infant stored human milk or formula.

Geriatric Use

In general, dose selection for an elderly patient should be cautious, reflecting the greater frequency of decreased hepatic, renal, or cardiac function, and of concomitant disease or other drug therapy.

In geriatric patients, monitoring for metronidazole associated adverse events is recommended (see CLINICAL PHARMACOLOGY, PRECAUTIONS). Decreased liver function in geriatric patients can result in increased concentrations of metronidazole that may necessitate adjustment of metronidazole dosage (see DOSAGE AND ADMINISTRATION).

Pediatric Use

Pediatric Patients Less than 4 Months of Age
The safety and effectiveness of Metronidazole Injection have been established for the treatment of intraabdominal infections in pediatric patients from birth to less than 4 months. Use of Metronidazole Injection in this age group is supported by evidence from data in adults with additional pharmacokinetic and safety data in pediatric patients from birth to less than 4 months of age.

A partially randomized, open-label, phase 2/3 study of intravenous Metronidazole Injection in combination with other intravenous antibacterial drugs was conducted in 62 preterm infants (≤ 33 weeks gestational age at birth, and postnatal age <121 days) and 55 late pre-term and term infants (≥ 34 weeks gestational age at birth, and postnatal age <121 days), with complicated intra-abdominal infections. The primary objective of this study was to evaluate the safety of metronidazole-containing regimens, which were administered for up to 10 days. The adverse reactions reported in patients receiving metronidazole-containing regimens were comparable to patients receiving other antibacterial regimens in the study and generally similar to adverse reactions described in adults.

The safety and effectiveness of Metronidazole Injection in pediatric patients less than 4 months of age have not been established for (1) the treatment of anaerobic infections other than intra-abdominal infections or for (2) prophylaxis for postoperative infections (see INDICATIONS AND USAGE, CLINICAL PHARMACOLOGY, Pediatric Patients and DOSAGE AND ADMINISTRATION).

Pediatric Patients 4 Months of Age and Older
The safety and effectiveness of Metronidazole Injection in pediatric patients 4 months of age and older have not been established.

ADVERSE REACTIONS

The following reactions have been reported during treatment with metronidazole formulations:

INFECTIONS AND INFESTATIONS: Vaginal candidiasis

BLOOD AND LYMPHATIC SYSTEM DISORDERS: Agranulocytosis, Leukopenia, Neutropenia, Thrombocytopenia, Eosinophilia

IMMUNE SYSTEM DISORDERS: Anaphylactic reaction, Hypersensitivity

METABOLISM AND NUTRITION DISORDERS: Decreased appetite

PSYCHIATRIC DISORDERS: Confusional state, Depression, Insomnia, Decreased libido

NERVOUS SYSTEM DISORDERS: Encephalopathy, Seizure, Neuropathy peripheral, Ataxia, Dizziness, Hypoesthesia, Paresthesia, Dysgeusia, Headache, Nystagmus, Aseptic meningitis, Somnolence, Dysarthria, Numbness, Syncope

EYE DISORDERS: Optic neuropathy, Saccadic eye movement

EAR AND LABYRINTH DISORDERS: Vertigo, tinnitus, hearing impairment, hearing loss

CARDIAC DISORDERS: QT prolongation has been reported, particularly when metronidazole was administered with drugs with the potential for prolonging the QT interval. Flattening of the T-wave may be seen in electrocardiographic tracings, Tachycardia, Palpitation

RESPIRATORY, THORACIC AND MEDIASTINAL DISORDERS: Dyspnea

GASTROINTESTINAL DISORDERS: Pancreatitis, Abdominal pain, Diarrhea, Nausea, Vomiting, Asthenia, Proctitis

HEPATOBILIARY DISORDERS: Hepatotoxicity/Liver Failure in patients with Cockayne syndrome (see CONTRAINDICATIONS), Jaundice

SKIN AND SUBCUTANEOUS DISORDERS: Toxic epidermal necrolysis, Swelling face, Pruritus, Urticaria, Hyperhidrosis, Erythema, Rash; Stevens-Johnson syndrome, Fixed drug eruption, Drug Reaction with Eosinophilia and Systemic Symptoms (DRESS), acute generalized exanthematous pustulosis (AGEP) (see WARNINGS)

MUSCULOSKELETAL AND CONNECTIVE TISSUE DISORDERS: Muscle spasms, Arthralgia, Myalgia

RENAL AND URINARY DISORDERS: Chromaturia, Dysuria

Hepatic: Cases of severe irreversible hepatotoxicity/acute liver failure, including cases with fatal outcomes with very rapid onset after initiation of systemic use of metronidazole, have been reported in patients with Cockayne Syndrome (latency from drug start to signs of liver failure as short as 2 days) (see CONTRAINDICATIONS)

REPRODUCTIVE: Dyspareunia

GENERAL DISORDERS AND ADMINISTRATION SITE CONDITIONS: Injection site reaction, Malaise, Face edema, Edema peripheral, Chest pain, Chills

INVESTIGATIONS: Hepatic enzyme increased.

Patients with Crohn's disease are known to have an increased incidence of gastrointestinal and certain extraintestinal cancers. There have been some reports in the medical literature of breast and colon cancer in Crohn's disease patients who have been treated with metronidazole at high doses for extended periods of time. A cause and effect relationship has not been established. Crohn's disease is not an approved indication for Metronidazole Injection.

OVERDOSAGE

Signs and symptoms of an overdose may include: nausea, vomiting, and neurotoxic effects, including ataxia, confusion, disorientation, seizures, and peripheral neuropathy.

Treatment of Overdosage

Symptomatic treatment is recommended. There is no specific antidote for an overdose of metronidazole. Discontinue metronidazole administration in the event of an overdose. Hemodialysis removes significant amounts of metronidazole and its metabolites from systemic circulation.

DOSAGE AND ADMINISTRATION

Dosage, rate of administration, and duration of treatment are to be individualized and depend upon the indication for use, the patient’s age, weight, clinical condition and concomitant treatment, and on the patient’s clinical and laboratory response to the treatment.

Recommended Dosage for the Treatment of Anaerobic Bacterial Infections

The recommended dosage schedule for adults for the treatment of anaerobic infections is presented in the Table 1:

Table 1. Recommended Dosage Schedule for the Treatment of Anaerobic Bacterial Infections in Adults
Loading Dose | 15 mg/kg infused intravenously over one hour (approximately 1 gram for a 70-kg adult).
Maintenance Dosage | 7.5 mg/kg infused intravenously over one hour every six hours (approximately 500 mg for a 70-kg adult). The first maintenance dose should be instituted six hours following the initiation of the loading dose.

Parenteral therapy may be changed to oral metronidazole therapy when conditions warrant, based upon the severity of the disease and the response of the patient to treatment with Metronidazole Injection. The usual adult oral dosage is 7.5 mg/kg every six hours (approximately 500 mg for a 70-kg adult).

A maximum of 4 grams should not be exceeded during a 24-hour period.

The usual duration of therapy is 7 to 10 days; however, infections of the bone and joint, lower respiratory tract and endocardium may require longer treatment.

Recommended Dosage for the Treatment of Intra-Abdominal Infections in Pediatric Patients Less than 4 Months of Age:

The recommended dosage schedule for pediatric patients less than 4 months of age for the treatment of intra-abdominal infections is described in Table 2 below. These dosage schedules achieve drug exposures in pediatric patients similar to adults treated with Metronidazole Injection for this indication.

Table 2. Recommended Dosage Schedule for the Treatment of Intra-Abdominal Infections in Pediatric Patients Less than 4 months of Age
Post-menstrual age (Completed weeks) | Loading Dose (mg/kg) | Maintenance Dose [The first maintenance dose is given 24 hours after the start of the loading dose.] (mg/kg) | Dosing interval (hours)
23 to <34 | 15 | 7.5 | 12
34 to 40 | 15 | 7.5 | 8
>40 to 48 | 15 | 7.5 | 6

Recommended Dosage in Patients with Severe Hepatic Impairment
For patients with severe hepatic impairment (Child-Pugh C), the metronidazole dose should be reduced by 50% (see CLINICAL PHARMACOLOGY and PRECAUTIONS).

Recommended Dosage in Patients Undergoing Hemodialysis

Hemodialysis removes significant amounts of metronidazole and its metabolites from systemic circulation. The clearance of metronidazole will depend on the type of dialysis membrane used, the duration of the dialysis session, and other factors. If the administration of metronidazole cannot be separated from a hemodialysis session, supplementation of metronidazole dosage following a hemodialysis session should be considered, depending on the patient’s clinical situation (see CLINICAL PHARMACOLOGY).

Dosage Considerations in Geriatric Patients

In elderly patients the pharmacokinetics of metronidazole may be altered and, therefore, monitoring of serum levels may be necessary to adjust the metronidazole dosage accordingly.

Recommended Prophylaxis Dosage

For surgical prophylactic use, to prevent postoperative infection in contaminated or potentially contaminated colorectal surgery, the recommended dosage schedule for adults is:

a. 15 mg/kg infused over 30 to 60 minutes and completed approximately one hour before surgery; followed by
b. 7.5 mg/kg infused over 30 to 60 minutes at 6 and 12 hours after the initial dose.

It is important that (1) administration of the initial preoperative dose be completed approximately one hour before surgery so that adequate drug levels are present in the serum and tissues at the time of initial incision, and (2) Metronidazole Injection be administered, if necessary, at 6-hour intervals to maintain effective drug levels. Prophylactic use of Metronidazole Injection should be limited to the day of surgery only, following the above guidelines.

Important Administration and Preparation Instructions

Caution: Metronidazole Injection is to be administered by slow intravenous drip infusion only, either as a continuous or intermittent infusion. Additives should not be introduced into Metronidazole Injection, unless compatibility is known. If used with a primary intravenous fluid system, the primary solution should be discontinued during metronidazole infusion. DO NOT USE EQUIPMENT CONTAINING ALUMINUM (e.g., NEEDLES, CANNULAE) THAT WOULD COME IN CONTACT WITH THE DRUG SOLUTION AS PRECIPITATES MAY FORM.

Metronidazole Injection is incompatible with (includes but is not limited to): Aztreonam, Cefamandole nafate, Cefoxitin, Penicillin G.

In the absence of compatibility studies, this medicinal product must not be mixed with other medicinal products (see DIRECTIONS FOR USE OF VIAFLEX PLUS PLASTIC CONTAINER).

Parenteral drug products should be inspected visually for particulate matter and discoloration prior to administration, whenever solution and container permit. Do not administer unless the solution is clear and the seal is intact.

HOW SUPPLIED

Metronidazole Injection, USP is supplied in 100 mL single dose plastic containers, each containing an iso-osmotic, buffered solution of 500 mg metronidazole as follows:

2B3423 NDC 72572-540-24 500 mg/100 mL

Store at controlled room temperature (77°F or 25°C) and protect from light during storage. Do not remove unit from overwrap until ready for use. The overwrap is a moisture barrier. The inner bag maintains the sterility of the product. After removing overwrap, check for minute leaks by squeezing inner bag firmly. If leaks are found, discard solution as sterility may be impaired.

DIRECTIONS FOR USE OF VIAFLEX PLUS PLASTIC CONTAINER

Metronidazole Injection is a ready-to-use iso-osmotic solution. No dilution or buffering is required. Do not refrigerate. Each container of Metronidazole Injection contains 14 mEq of sodium.

Do not connect flexible plastic containers in series in order to avoid air embolism due to possible residual air contained in the primary container.

Pressurizing intravenous solutions contained in flexible plastic containers to increase flow rates can result in air embolism if the residual air in the container is not fully evacuated prior to administration.

Use of a vented intravenous administration set with the vent in the open position could result in air embolism. Vented intravenous administration sets with the vent in the open position should not be used with flexible plastic containers.

Discard any unused portion.

For single dose only.

To open

Tear overwrap down side at slit and remove solution container. Visually inspect the container. If the outlet port protector is damaged, detached, or not present, discard container as solution path sterility may be impaired. Some opacity of the plastic due to moisture absorption during the sterilization process may be observed. This is normal and does not affect the solution quality or safety. The opacity will diminish gradually. Check for leaks. Do not add supplementary medication.

Preparation for Administration

1. Suspend container from eyelet support.
2. Remove protector from outlet port at bottom of container.
3. Attach administration set. Refer to complete directions accompanying set.

Distributed by:
Civica, Inc.
Lehi, Utah 84048

Manufactured by:
Baxter Healthcare Corporation
Deerfield, IL 60015 USA
Made in Puerto Rico
Printed in USA

Baxter and Viaflex are registered trademarks of Baxter International Inc. and its subsidiaries.

07-19-01-0274
Rev. 4/2025

Civica Logo

PACKAGE LABEL - PRINCIPAL DISPLAY PANEL

Container Label

LOT
EXP

NDC 72572-540-24
Rx Only

Metronidazole
Metronidazole Injection USP

500 mg per 100 mL
(5 mg / mL)

100 ML STERILE SINGLE DOSE
CONTAINER EACH 100 mL CONTAINS 500 mg
METRONIDAZOLE USP 790 mg
SODIUM CHLORIDE USP 47.6 mg DIBASIC
SODIUM PHOSPHATE DRIED USP 22.9 mg
CITRIC ACID ANHYDROUS USP PH 5.5
(4.5 TO 7.0) OSMOLARITY 310 mOsmoL/L
(CALC) USUAL DOSAGE SEE INSERT DO NOT
ADD SUPPLEMENTARY MEDICATION
STORE IN MOISTURE BARRIER OVERWRAP AT ROOM
TEMPERATURE (77°F OR 25°C) AND PROTECT FROM
LIGHT DURING STORAGE

Mfd for: Civica, Inc., Lehi, UT 84043
Mfd by: Baxter Healthcare Corp.
Deerfield, IL 60015
Made in Puerto Rico
07-25-00-5756
2B3423

Civica Logo